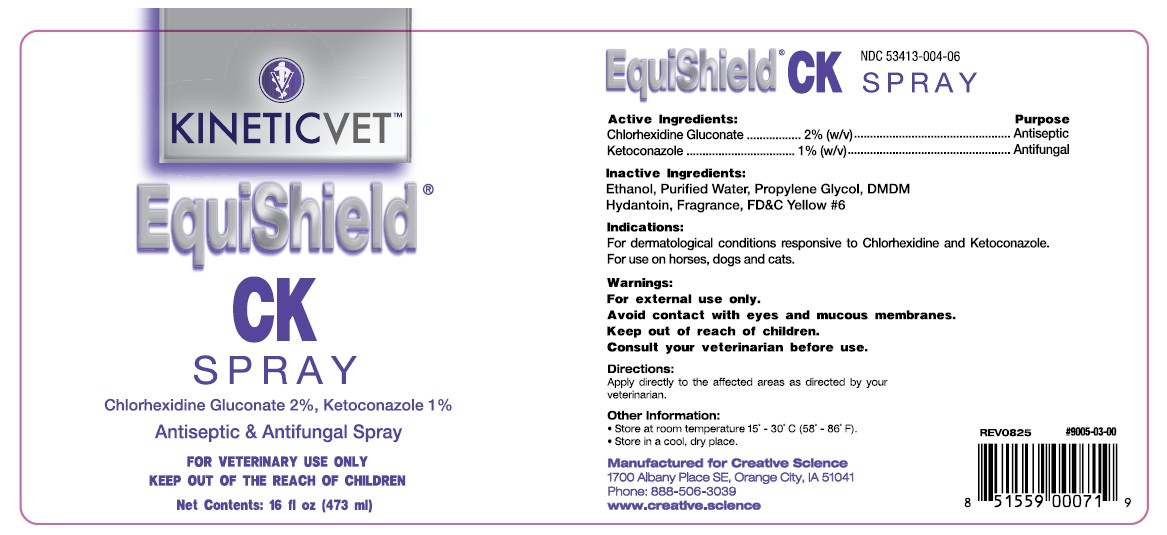 DRUG LABEL: EquiShield CK
NDC: 53413-004 | Form: SPRAY
Manufacturer: Creative Science
Category: animal | Type: OTC ANIMAL DRUG LABEL
Date: 20251206

ACTIVE INGREDIENTS: CHLORHEXIDINE GLUCONATE 2 g/100 mL; KETOCONAZOLE 1 g/100 mL

EquiShield CK Spray

Active Ingredients: Purpose

Chlorhexidine Gluconate 2% (w/v) Antiseptic
Ketoconazole 1% (w/v) Antifungal

Inactive Ingredients:

Ethanol, Purified Water, Propylene Glycol, DMDM Hydantoin, Fragrance, FD&C Yellow #6

Indications:

For dermatological conditions responsive to Chlorhexidine and Ketoconazole. For use on horses, dogs and cats.

Warnings:

For external use only.

Avoid contact with eyes and mucous membranes.

Keep out of reach of children.

Consult your veterinarian before use.

Directions:

Apply directly to the affected areas as directed by your veterinarian.

Other Information:

• Store at room temperature 15˚ - 30˚C (58˚ - 86˚F).
• Store in a cool, dry place.

NDC 53413-004-06

Manufactured for Creative Science

1700 Albany Place SE, Orange City, IA 51041

Phone: 888-506-3039

www.creative.science

PACKAGE LABEL

KINETIC™VET

EquiShield® CK Spray

Chlorhexidine Gluconate 2%, Ketaconazole 1%

Antiseptic & Antifungal Spray

FOR VETERINARY USE ONLY

KEEP OUT OF THE REACH OF CHILDREN

Net Contents: 16 fl oz (473 ml)

Add image transcription here...